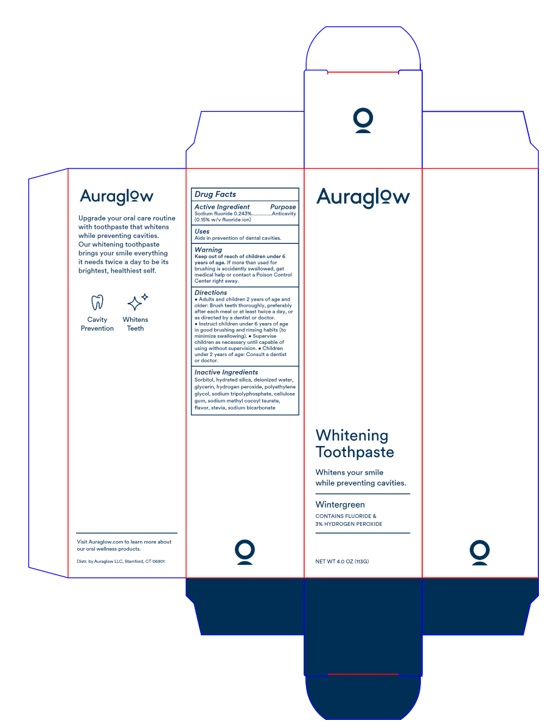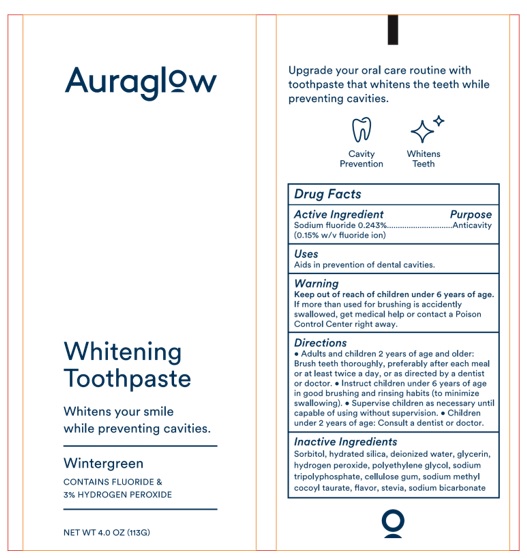 DRUG LABEL: Auraglow Whitening
NDC: 81740-001 | Form: PASTE, DENTIFRICE
Manufacturer: Auraglow LLC
Category: otc | Type: HUMAN OTC DRUG LABEL
Date: 20221107

ACTIVE INGREDIENTS: SODIUM FLUORIDE 2.43 mg/1 g
INACTIVE INGREDIENTS: SORBITOL; HYDRATED SILICA; WATER; GLYCERIN; HYDROGEN PEROXIDE; POLYETHYLENE GLYCOL 1600; SODIUM TRIPOLYPHOSPHATE; CARBOXYMETHYLCELLULOSE SODIUM, UNSPECIFIED; SODIUM METHYL COCOYL TAURATE; STEVIA REBAUDIUNA LEAF; SODIUM BICARBONATE

Auraglow Whitening Toothpaste

Drug Facts

Active ingredient

Sodium fluoride 0.243%

(0.15% w/v fluoride ion)

Purpose Anticavity

INDICATIONS AND USAGE

Use Aids in prevention of dental cavities.

Warnings

Keep out of reach of children under 6 years of age.

If more than used for brushing is accidentally swallowed, get

medical help or contact a Poison Control Center right away.

Directions

• Adults and children 2 years of age and
older: Brush teeth thouroughly, preferably after each meal or
at least twice a day, or as directed by a dentist or doctor.
• Instruct children under 6 years of age in good brushing
and rinsing habits (to minimize swallowing). • Supervise
children as necessary until capable of using without supervision.

• Children under 2 years of age: Consult a dentist or doctor.

Inactive Ingredients

Sorbitol, hydrated silica, deionized water,

glycerin, hydrogen peroxide, polyethylene

glycol, sodium tripolyphosphate, cellulose

gum, sodium methyl cocoyl tautate,

flavor, stevia, sodium bicarbonate

Package Labeling

Auraglow

Whitening Toothpaste

Wintergreen

CONTAINS FLUORIDE &

3% HYDROGEN PEROXIDE

NET WT 4.0 OZ (113G)

Distr. by Auraglow LLC, Stamford, CT 06901

res